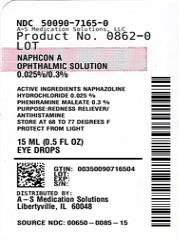 DRUG LABEL: Naphcon A 
NDC: 50090-7165 | Form: SOLUTION/ DROPS
Manufacturer: A-S Medication Solutions
Category: otc | Type: HUMAN OTC DRUG LABEL
Date: 20240822

ACTIVE INGREDIENTS: NAPHAZOLINE HYDROCHLORIDE 0.25 mg/1 mL; PHENIRAMINE MALEATE 3 mg/1 mL
INACTIVE INGREDIENTS: Benzalkonium Chloride; Boric Acid; Edetate Disodium; Water; Sodium Borate; Sodium Chloride; Sodium Hydroxide; Hydrochloric Acid

Drug Facts

ACTIVE INGREDIENT

Active ingredients | Purpose
Naphazoline hydrochloride 0.025% | Redness reliever
Pheniramine maleate 0.3% | Antihistamine

Uses

for the temporary relief of redness and itching of the eye(s) due to:

- ragweed
- pollen
- grass
- animal dander and hair

Warnings

For external use only

Do not use

- if you are sensitive to any ingredient in this product
- if this solution changes color or becomes cloudy

Ask a doctor before use if you have

- narrow angle glaucoma
- heart disease
- high blood pressure
- trouble urinating

When using this product

- pupils may become enlarged temporarily causing light sensitivity
- overuse may cause more eye redness
- remove contact lenses before using
- to avoid contamination, do not touch tip of container to any surface
- replace cap after each use

Stop use and ask a doctor if

- you feel eye pain
- changes in vision occur
- redness or irritation of the eye(s) gets worse or lasts more than 72 hours

Keep out of the reach of children.

If swallowed, get medical help or contact a Poison Control Center right away. Accidental swallowing by infants and children may lead to coma and marked reduction in body temperature.

Directions

- adults and children 6 years and over: put 1 or 2 drops in the affected eye(s) up to 4 times daily
- children under 6 years: ask a doctor

Other information

- store at 20°-25°C (68°-77°F)
- protect from light

Inactive ingredients

benzalkonium chloride, boric acid, edetate disodium, purified water, sodium borate, sodium chloride, sodium hydroxide and/or hydrochloric acid

Questions?

In the U.S. call 1-800-757-9195 or visit www.alcon.com

HOW SUPPLIED

Product: 50090-7165

NDC: 50090-7165-0 15 mL in a BOTTLE / 1 in a CARTON